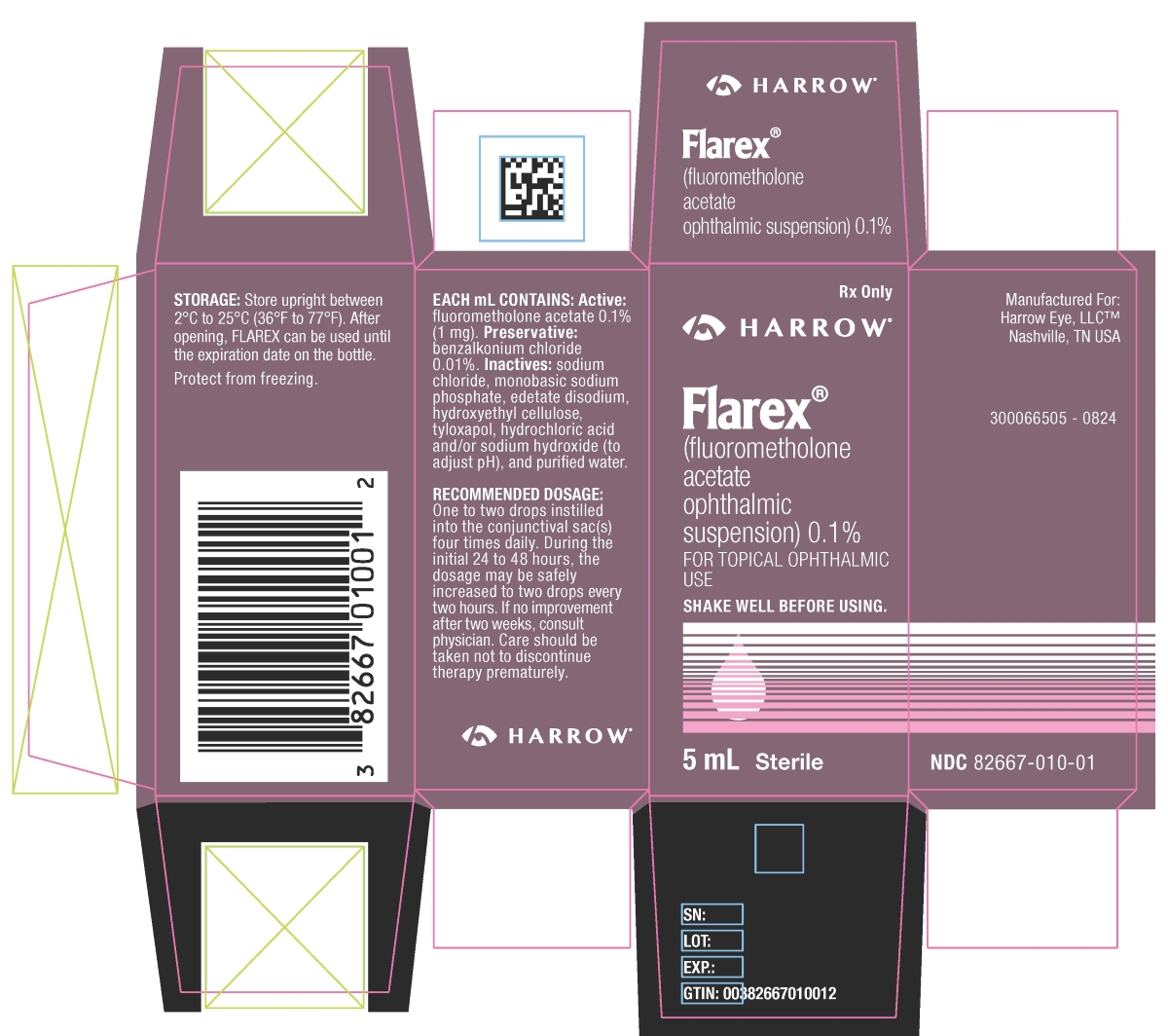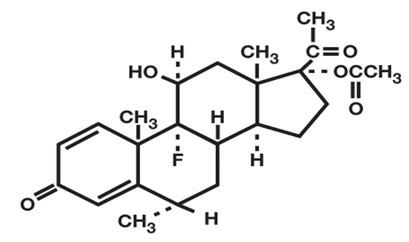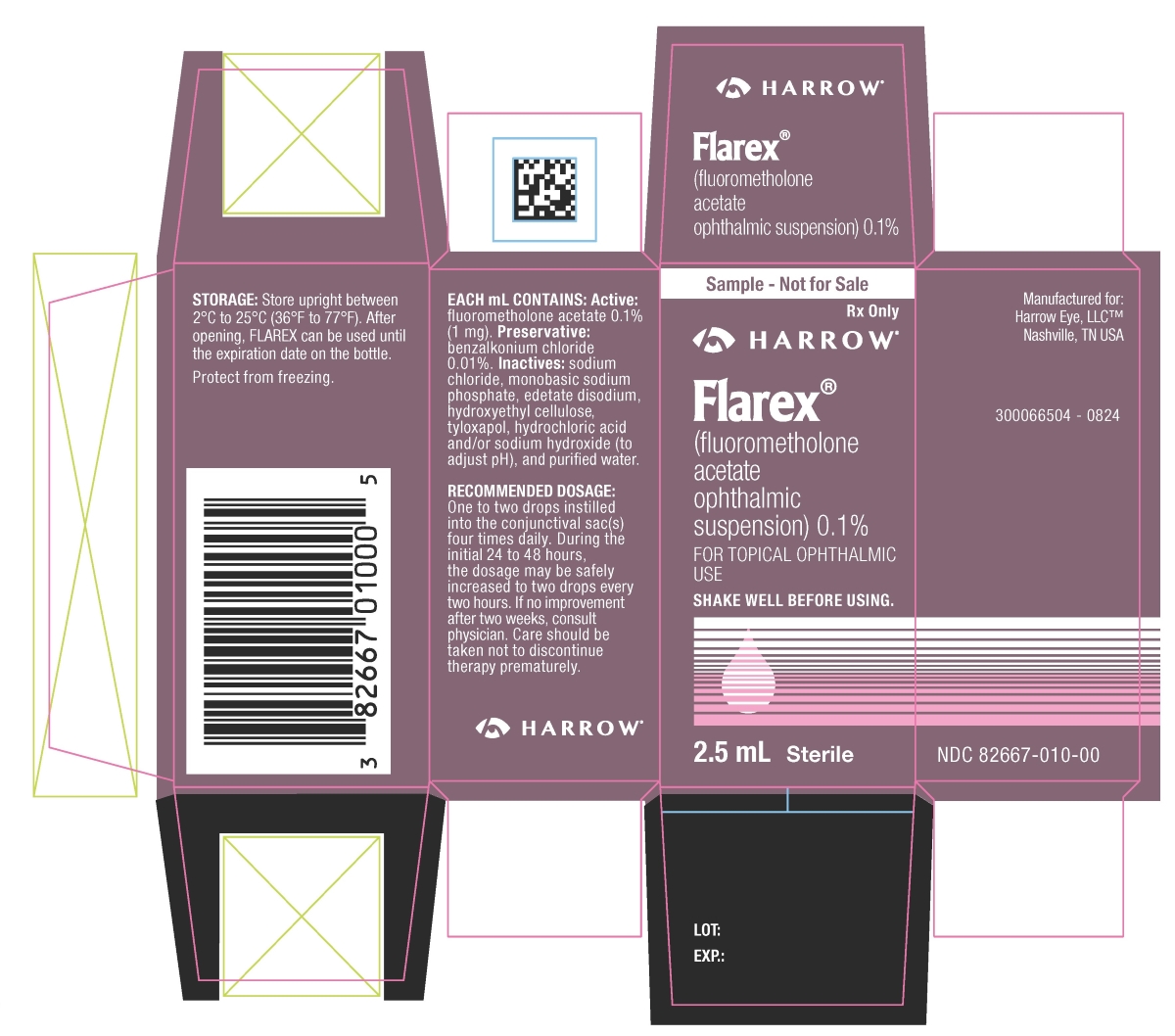 DRUG LABEL: Flarex
NDC: 82667-010 | Form: SUSPENSION/ DROPS
Manufacturer: Harrow Eye, LLC
Category: prescription | Type: HUMAN PRESCRIPTION DRUG LABEL
Date: 20250331

ACTIVE INGREDIENTS: FLUOROMETHOLONE ACETATE 1 mg/1 mL
INACTIVE INGREDIENTS: BENZALKONIUM CHLORIDE; SODIUM CHLORIDE; SODIUM PHOSPHATE, MONOBASIC, UNSPECIFIED FORM; EDETATE DISODIUM; HYDROXYETHYL CELLULOSE (2000 MPA.S AT 1%); TYLOXAPOL; HYDROCHLORIC ACID; SODIUM HYDROXIDE; WATER

FLAREX®(fluorometholone acetate ophthalmic suspension) 0.1%
Sterile

DESCRIPTION

FLAREX®(fluorometholone acetate ophthalmic suspension) 0.1% is a corticosteroid prepared as a sterile topical ophthalmic suspension. The active ingredient, fluorometholone acetate, is a white to creamy white powder with an empirical formula of C24H31FO5and a molecular weight of 418.5. Its chemical name is 9-fluoro-11β, 17-dihydroxy-6α-methylpregna-1, 4-diene-3, 20-dione 17-acetate. The chemical structure of Fluorometholone Acetate is presented below:

Each mL of FLAREX (fluorometholone acetate ophthalmic suspension) 0.1% contains: Active:fluorometholone acetate 1 mg (0.1%). Preservative:benzalkonium chloride 0.01%. Inactives:sodium chloride, monobasic sodium phosphate, edetate disodium, hydroxyethyl cellulose, tyloxapol, hydrochloric acid and/or sodium hydroxide (to adjust pH), and purified water. The pH of the suspension is approximately 7.3, with an osmolality of approximately 300 mOsm/kg.

CLINICAL PHARMACOLOGY

Corticosteroids suppress the inflammatory response to inciting agents of mechanical, chemical or immunological nature. No generally accepted explanation of this steroid property has been advanced. Corticosteroids cause a rise in intraocular pressure (IOP) in susceptible individuals. In a small study, FLAREX (fluorometholone acetate ophthalmic suspension) 0.1% demonstrated a significantly longer average time to produce a rise in IOP than did dexamethasone phosphate; however, the ultimate magnitude of the rise was equivalent for both drugs and in a small percentage of individuals a significant rise in IOP occurred within three days.

INDICATIONS AND USAGE

FLAREX (fluorometholone acetate ophthalmic suspension) 0.1% is indicated for use in the treatment of steroid responsive inflammatory conditions of the palpebral and bulbar conjunctiva, cornea, and anterior segment of the eye.

CONTRAINDICATIONS

Contraindicated in acute superficial herpes simplex keratitis, vaccinia, varicella, and most other viral diseases of cornea and conjunctiva; mycobacterial infection of the eye; fungal diseases; acute purulent untreated infections, which like other diseases caused by microorganisms, may be masked or enhanced by the presence of the steroid; and in those persons who have known hypersensitivity to any component of this preparation.

WARNINGS

FOR TOPICAL OPHTHALMIC USE. NOT FOR INJECTION. Use in the treatment of herpes simplex infection requires great caution. Prolonged use may result in glaucoma, damage to the optic nerve, defect in visual acuity and visual field, cataract formation and/or may aid in the establishment of secondary ocular infections from pathogens due to suppression of host response. Acute purulent infections of the eye may be masked or exacerbated by presence of steroid medication. Topical ophthalmic corticosteroids may slow corneal wound healing. In those diseases causing thinning of the cornea or sclera, perforation has been known to occur with chronic use of topical steroids. If these products are used for 10 days or longer, intraocular pressure (IOP) should be routinely monitored even though it may be difficult in children and uncooperative patients.

PRECAUTIONS

General

Fungal infections of the cornea are particularly prone to develop coincidentally with long-term local steroid application. Fungus invasion must be considered in any persistent corneal ulceration where a steroid has been used or is in use.

Prescription Guidelines

The initial prescription and renewal of the medication order should be made by a physician only after examination of the patient with the aid of magnification, such as slit lamp biomicroscopy, and, where appropriate, fluorescein staining. If signs and symptoms fail to improve after 2 days, the patient should be re-evaluated.

Not more than one bottle should be prescribed initially, and the prescription should not be refilled without further evaluation.

Information for Patients

Do not touch dropper tip to any surface, as this may contaminate the suspension. The preservative in FLAREX®(fluorometholone acetate ophthalmic suspension) 0.1%, benzalkonium chloride, may be absorbed by soft contact lenses. Contact lenses should be removed during instillation of FLAREX (fluorometholone acetate ophthalmic suspension) 0.1% but may be reinserted 15 minutes after instillation.

Patients should be advised that their vision may be temporarily blurred following dosing with FLAREX®(fluorometholone acetate ophthalmic suspension) 0.1%. Care should be exercised in operating machinery or driving a motor vehicle.

Carcinogenesis, Mutagenesis, Impairment of Fertility

No studies have been conducted in animals or in humans to evaluate the possibility of these effects with fluorometholone.

Pregnancy

TERATOGENIC EFFECTS

Fluorometholone has been shown to be embryocidal and teratogenic in rabbits when administered at low multiples of the human ocular dose. Fluorometholone was applied ocularly to rabbits daily on days 6-18 of gestation, and dose-related fetal loss and fetal abnormalities including cleft palate, deformed rib cage, anomalous limbs and neural abnormalities such as encephalocele, craniorachischisis, and spina bifida were observed. There are no adequate and well controlled studies of fluorometholone in pregnant women, and it is not known whether fluorometholone can cause fetal harm when administered to a pregnant woman. Fluorometholone should be used during pregnancy only if the potential benefit justifies the potential risk to the fetus.

Nursing Mothers

Systemically administered corticosteroids appear in human milk and could suppress growth, interfere with endogenous corticosteroid production, or cause other untoward effects. It is not known whether topical administration of corticosteroids could result in sufficient systemic absorption to produce detectable quantities in human milk. Because many drugs are excreted in human milk, caution should be exercised when FLAREX (fluorometholone acetate ophthalmic suspension) 0.1%, is administered to a nursing woman.

Pediatric Use

Safety and effectiveness in pediatric patients have not been established.

Geriatric Use

No overall differences in safety or effectiveness have been observed between elderly and younger patients.

ADVERSE REACTIONS

Glaucoma with optic nerve damage, visual acuity and field defects, cataract formation, secondary ocular infection following suppression of host response, and perforation of the globe may occur.

Postmarketing Experience

The following reaction has been identified during post-marketing use of FLAREX ®(fluorometholone acetate ophthalmic suspension) 0.1% in clinical practice. Because reactions are reported voluntarily from a population of unknown size, estimates of frequency cannot be made. The reaction, which has been chosen for inclusion due to either its seriousness, frequency of reporting, possible causal connection to FLAREX, or a combination of these factors, includes: dysgeusia.

The following rare adverse reactions have been reported: Cushing's syndrome and adrenal suppression may occur after very frequent use of topical ophthalmic corticosteroids, particularly in very young children.

DOSAGE AND ADMINISTRATION

Shake Well Before Using.One to two drops instilled into the conjunctival sac(s) four times daily. During the initial 24 to 48 hours the dosage may be safely increased to two drops every two hours. If no improvement after two weeks, consult physician. Care should be taken not to discontinue therapy prematurely.

Not more than one bottle should be prescribed initially, and the prescription should not be refilled without further evaluation [see PRECAUTIONS] .

HOW SUPPLIED

FLAREX (fluorometholone acetate ophthalmic suspension) 0.1% is supplied in white low density polyethylene (LDPE) bottles, with natural LDPE dispensing plugs and pink polypropylene closures. The product is supplied as 5 mL in an 8 mL bottle.

5 mL: | NDC 82667-010-01

STORAGE

Store upright between 2°C to 25°C (36°F to 77°F). After opening, FLAREX can be used until the expiration date on the bottle.

Protect from freezing.

Manufactured for:
Harrow Eye, LLCTM
Nashville, TN USA
Revised: 09/2024

PRINCIPAL DISPLAY PANEL - 2.5 mL Bottle Carton

Harrow ®

Flarex®

(fluorometholone
acetate
ophthalmic
suspension) 0.1 %

FOR TOPICAL OPHTHALMIC
USE

2.5mL
Sterile

PRINCIPAL DISPLAY PANEL - 5 mL Bottle Carton

Harrow®

Flarex®
(fluorometholone
acetate
ophthalmic
suspension) 0.1 %

FOR TOPICAL OPHTHALMIC
USE

5 mL
Sterile